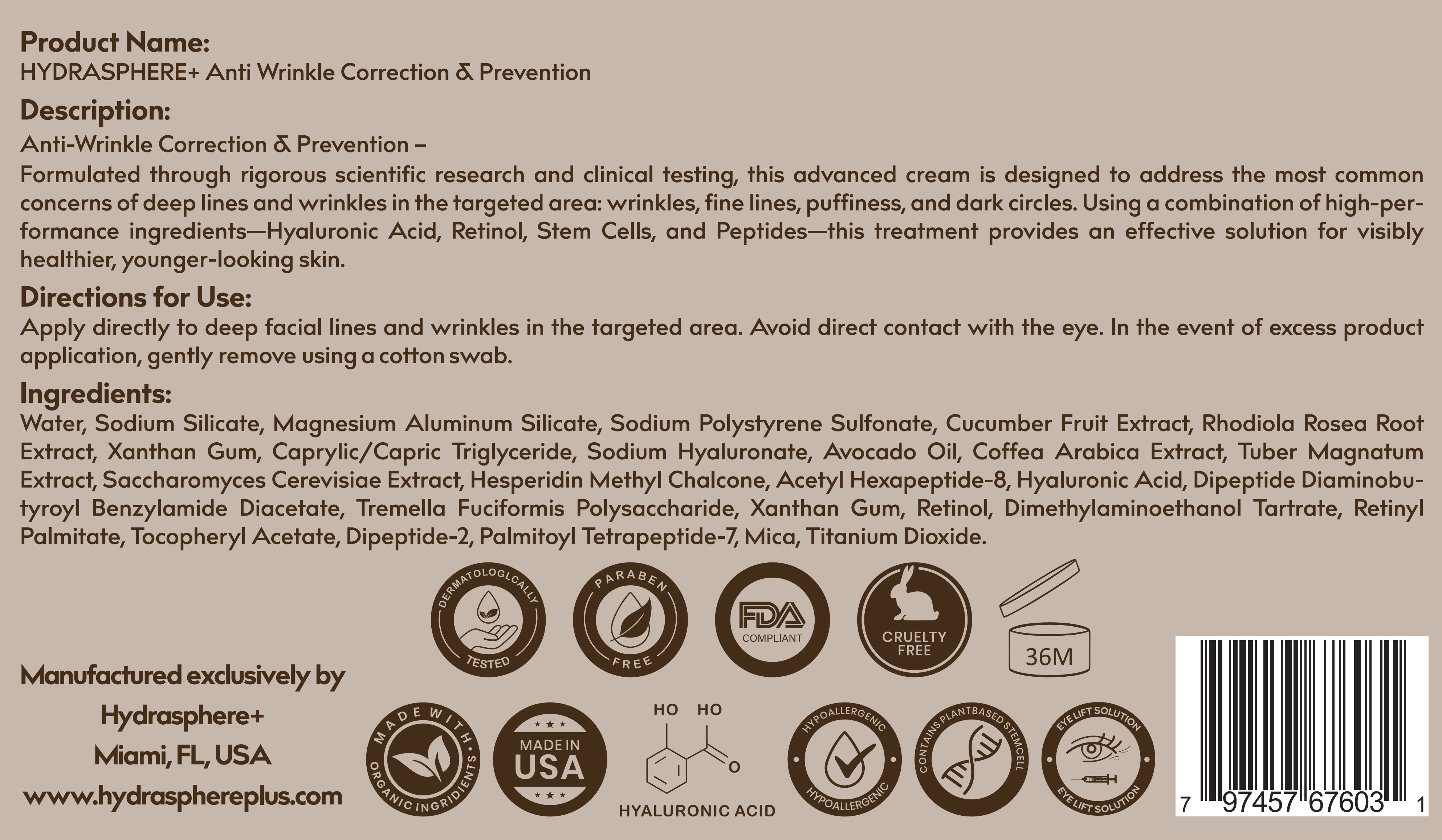 DRUG LABEL: HYDRASPHERE PLUS
NDC: 85579-003 | Form: CREAM
Manufacturer: HYDRASPHERE PLUS LLC
Category: otc | Type: HUMAN OTC DRUG LABEL
Date: 20250429

ACTIVE INGREDIENTS: RETINOL 1 g/100 g
INACTIVE INGREDIENTS: SODIUM SILICATE; WATER; MAGNESIUM ALUMINUM SILICATE; SODIUM POLYSTYRENE SULFONATE; CUCUMBER FRUIT OIL; RHODIOLA ROSEA ROOT; XANTHAN GUM; CAPRYLIC/CAPRIC TRIGLYCERIDE; SODIUM HYALURONATE; AVOCADO OIL; COFFEA ARABICA FRUIT; TUBER MAGNATUM WHOLE; SACCHAROMYCES CEREVISIAE; HESPERIDIN METHYL CHALCONE; ACETYL HEXAPEPTIDE-8; HYALURONIC ACID; DIPEPTIDE DIAMINOBUTYROYL BENZYLAMIDE DIACETATE; TREMELLA FUCIFORMIS WHOLE; DIMETHYLAMINOETHANOL TARTRATE; RETINYL PALMITATE; DIPEPTIDE-2; PALMITOYL TETRAPEPTIDE-7; MICA; TITANIUM DIOXIDE

active

RETINOL

inactive

Water
Magnesium Aluminum Silicate
Sodium Polystyrene Sulfonate
Cucumber Fruit Extract
Rhodiola Rosea Root Extract
Xanthan Gum
Caprylic/Capric Triglyceride
Sodium Hyaluronate
Avocado Oil
Coffea Arabica Extract
Tuber Magnatum Extract
Saccharomyces Cerevisiae Extract
Hesperidin Methyl Chalcone
Sodium Silicate
Hyaluronic Acid
Dipeptide Diaminobutyroyl Benzylamide Diacetate
Tremella Fuciformis Polysaccharide
Xanthan Gum
ACETYL HEXAPEPTIDE-8
Dimethylaminoethanol Tartrate
Retinyl Palmitate
Tocopheryl Acetate
Dipeptide-2
Palmitoyl Tetrapeptide-7
Mica
Titanium Dioxide

PURPOSE

Anti-Wrinkle Correction & Prevention –
Formulated through rigorous scientific research and clinical testing, this advanced cream is designed to address the most common concerns of deep lines and wrinkles in the targeted area: wrinkles, fine lines, puffiness, and dark circles. Using a combination of high-performance ingredients—Hyaluronic Acid, Retinol, Stem Cells, and Peptides—this treatment provides an effective solution for visibly healthier, younger-looking skin.

WARNINGS and PRECAUTIONS:

Keep out of reach of children.For external use only.Avoid contact with eyes ormucous membranes.Perform a patch test before firstuse. lf irritation occurs,discontinue use.May increase sun sensitivityuse SPF.

PREGAUTIONS:

Avoid contact with eyes ormucous membranes.

Directions for Use:

Apply directly to deep facial lines and wrinkles in the targeted area. Avoid direct contact with the eye. In the event of excess product application, gently remove using a cotton swab.

WARNINGS G PREGAUTIONS:

Keep out of reach of children.

Directions for Use:

Apply directly to deep facial lines and wrinkles in the targeted area. Avoid direct contact with the eye. In the event of excess product application, gently remove using a cotton swab.

Directions for Use:

Product Name:
HYDRASPHERE+ Anti Wrinkle Correction & Prevention

Directions for Use:

Apply directly to deep facial lines and wrinkles in the targeted area. Avoid direct contact with the eye. In the event of excess product application, gently remove using a cotton swab.

WARNINGS G PREGAUTIONS

Perform a patch test before firstuse. lf irritation occurs,discontinue use.

PACKAGE LABEL

Product Name:
HYDRASPHERE+ Anti Wrinkle Correction & Prevention

Description:
Anti-Wrinkle Correction & Prevention –
Formulated through rigorous scientific research and clinical testing, this advanced cream is designed to address the most common concerns of deep lines and wrinkles in the targeted area: wrinkles, fine lines, puffiness, and dark circles. Using a combination of high-performance ingredients—Hyaluronic Acid, Retinol, Stem Cells, and Peptides—this treatment provides an effective solution for visibly healthier, younger-looking skin.

Directions for Use:
Apply directly to deep facial lines and wrinkles in the targeted area. Avoid direct contact with the eye. In the event of excess product application, gently remove using a cotton swab.

Ingredients:
Water
Sodium Silicate
Magnesium Aluminum Silicate
Sodium Polystyrene Sulfonate
Cucumber Fruit Extract
Rhodiola Rosea Root Extract
Xanthan Gum
Caprylic/Capric Triglyceride
Sodium Hyaluronate
Avocado Oil
Coffea Arabica Extract
Tuber Magnatum Extract
Saccharomyces Cerevisiae Extract
Hesperidin Methyl Chalcone
Acetyl Hexapeptide-8
Hyaluronic Acid
Dipeptide Diaminobutyroyl Benzylamide Diacetate
Tremella Fuciformis Polysaccharide
Xanthan Gum
Retinol
Dimethylaminoethanol Tartrate
Retinyl Palmitate
Tocopheryl Acetate
Dipeptide-2
Palmitoyl Tetrapeptide-7
Mica
Titanium Dioxide